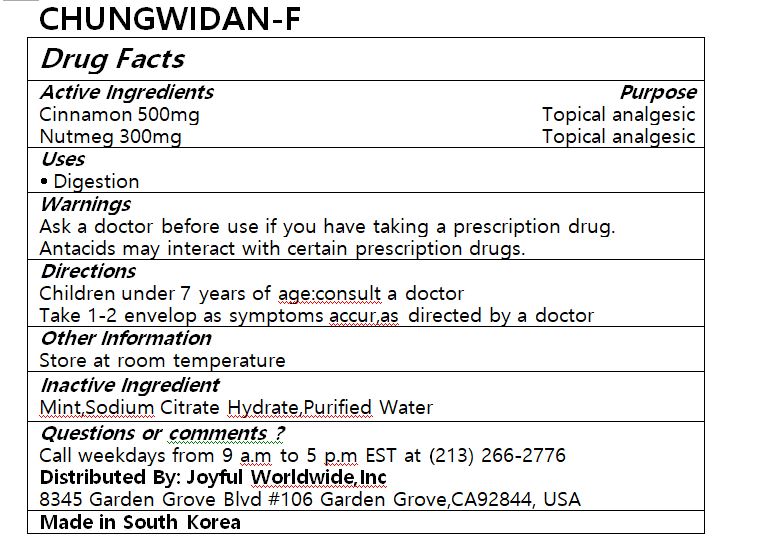 DRUG LABEL: CHUNGWIDAN-F
NDC: 72988-0029 | Form: LIQUID
Manufacturer: Lydia Co., Ltd.
Category: otc | Type: HUMAN OTC DRUG LABEL
Date: 20220605

ACTIVE INGREDIENTS: CINNAMON 500 mg/30 mL; NUTMEG 300 mg/30 mL
INACTIVE INGREDIENTS: MINT; SODIUM CITRATE; WATER

ACTIVE INGREDIENT

cinnamon, nutmeg

PURPOSE

digestion

Keep out of reach of children

INDICATIONS AND USAGE

Children under 7 years of age:consult a doctor

Take 1-2 envelop as symptoms accur,as directed by a doctor

Ask a doctor before use if you have taking a prescription drug.

Antacids may interact with certain prescription drugs.

INACTIVE INGREDIENT

Mint,Sodium Citrate Hydrate,Purified Water

DOSAGE AND ADMINISTRATION

for oral use